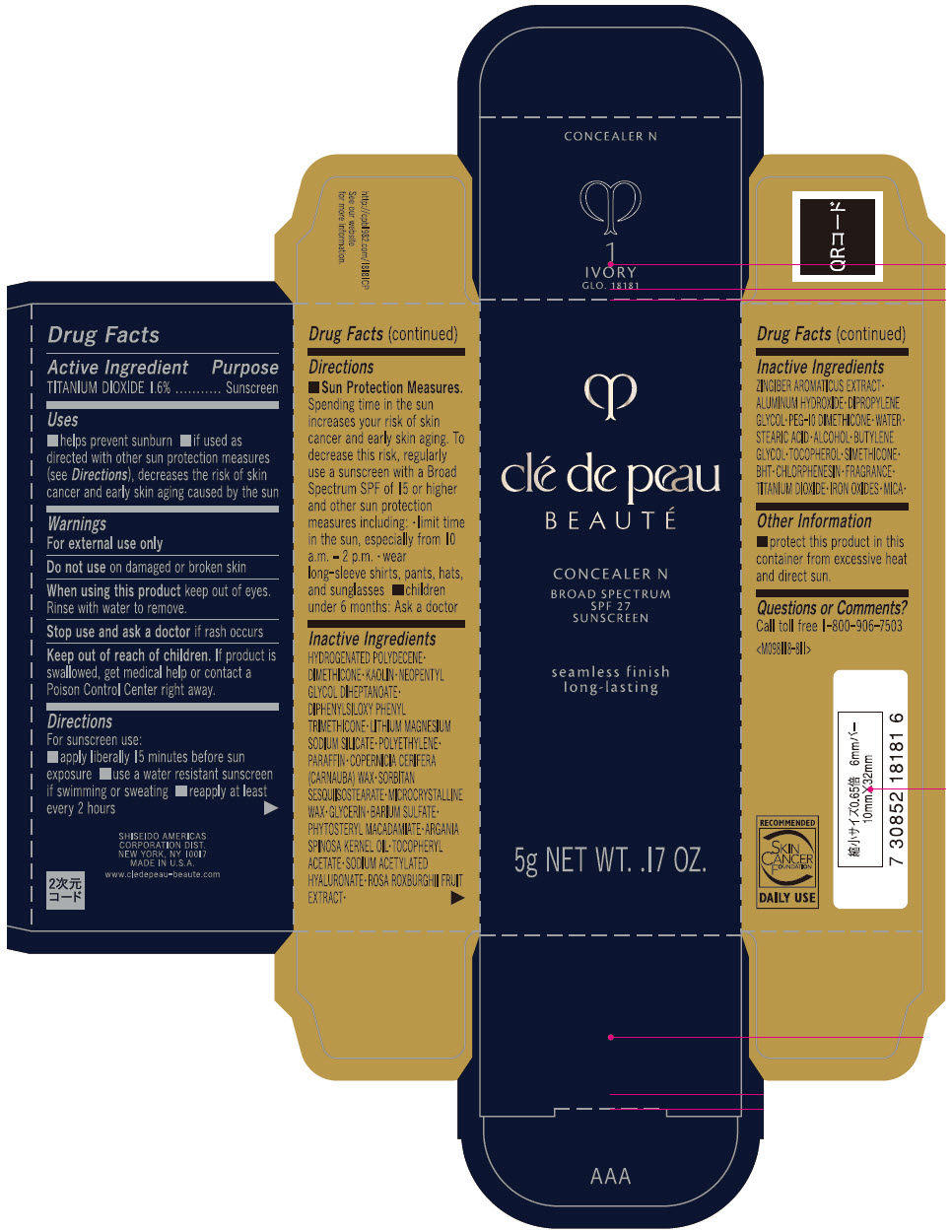 DRUG LABEL: cle de peau BEAUTE CONCEALER N

NDC: 58411-658 | Form: STICK
Manufacturer: SHISEIDO AMERICAS CORPORATION
Category: otc | Type: HUMAN OTC DRUG LABEL
Date: 20260105

ACTIVE INGREDIENTS: TITANIUM DIOXIDE 80 mg/5 g
INACTIVE INGREDIENTS: HYDROGENATED POLYDECENE TYPE I; DIMETHICONE; KAOLIN; NEOPENTYL GLYCOL DIHEPTANOATE; DIPHENYLSILOXY PHENYL TRIMETHICONE; LAPONITE; HIGH DENSITY POLYETHYLENE; PARAFFIN; CARNAUBA WAX; SORBITAN SESQUIISOSTEARATE; MICROCRYSTALLINE WAX; GLYCERIN; BARIUM SULFATE; PHYTOSTERYL MACADAMIATE; ARGAN OIL; .ALPHA.-TOCOPHEROL ACETATE, DL-; SODIUM ACETYLATED HYALURONATE; ROSA ROXBURGHII FRUIT; ALUMINUM HYDROXIDE; DIPROPYLENE GLYCOL; PEG-10 DIMETHICONE (600 CST); WATER; STEARIC ACID; ALCOHOL; BUTYLENE GLYCOL; .ALPHA.-TOCOPHEROL; BUTYLATED HYDROXYTOLUENE; CHLORPHENESIN; FERRIC OXIDE RED; FERRIC OXIDE YELLOW; FERROSOFERRIC OXIDE; MICA

clé de peau BEAUTÉ CONCEALER N

Drug Facts

Active ingredients

TITANIUM DIOXIDE 1.6%

Purpose

Sunscreen

Uses

- helps prevent sunburn
- if used as directed with other sun protection measures (see Directions), decreases the risk of skin cancer and early skin aging caused by the sun

Warnings

For external use only

Do not use on damaged or broken skin

WHEN USING

When using this productkeep out of eyes. Rinse with water to remove.

Stop use and ask a doctorif rash occurs.

Keep out of reach of children.If product is swallowed, get medical help or contact a Poison Control Center right away.

Directions

For sunscreen use:

- apply liberally 15 minutes before sun exposure
- use a water resistant sunscreen if swimming or sweating
- reapply at least every 2 hours
- Sun Protection Measures.
  Spending time in the sun increases your risk of skin cancer and early skin aging. To decrease this risk, regularly use a sunscreen with a broad spectrum SPF of 15 or higher and other sun protection measures including:
  - limit time in the sun, especially from 10 a.m. – 2 p.m.
  - wear long-sleeve shirts, pants, hats, and sunglasses
  - children under 6 months: Ask a doctor

Inactive Ingredients

HYDROGENATED POLYDECENE•DIMETHICONE•KAOLIN•NEOPENTYL GLYCOL DIHEPTANOATE•DIPHENYLSILOXY PHENYL TRIMETHICONE•LITHIUM MAGNESIUM SODIUM SILICATE•POLYETHYLENE•PARAFFIN•COPERNICIA CERIFERA (CARNAUBA) WAX•SORBITAN SESQUIISOSTEARATE•MICROCRYSTALLINE WAX•GLYCERIN•BARIUM SULFATE•PHYTOSTERYL MACADAMIATE•ARGANIA SPINOSA KERNEL OIL•TOCOPHERYL ACETATE•SODIUM ACETYLATED HYALURONATE•ROSA ROXBURGHII FRUIT EXTRACT•ZINGIBER AROMATICUS EXTRACT•ALUMINUM HYDROXIDE•DIPROPYLENE GLYCOL•PEG-10 DIMETHICONE•WATER•STEARIC ACID•ALCOHOL•BUTYLENE GLYCOL•TOCOPHEROL•SIMETHICONE•BHT•CHLORPHENESIN•FRAGRANCE•TITANIUM DIOXIDE•IRON OXIDES•MICA•

Other information

Protect this product in this container from excessive heat and direct sun.

Questions or comments?

Call toll free 1-800-906-7503

PRINCIPAL DISPLAY PANEL - 5 g Cartridge Carton - 1

clé de peau
BEAUTÉ

CONCEALER N
BROAD SPECTRUM
SPF 27
SUNSCREEN

seamless finish
long-lasting

5g NET WT. .17 OZ.

PRINCIPAL DISPLAY PANEL - 5 g Cartridge Carton - 2

clé de peau
BEAUTÉ

CONCEALER N
BROAD SPECTRUM
SPF 27
SUNSCREEN

seamless finish
long-lasting

5g NET WT. .17 OZ.

PRINCIPAL DISPLAY PANEL - 5 g Cartridge Carton - 3

clé de peau
BEAUTÉ

CONCEALER N
BROAD SPECTRUM
SPF 27
SUNSCREEN

seamless finish
long-lasting

5g NET WT. .17 OZ.

PRINCIPAL DISPLAY PANEL - 5 g Cartridge Carton - 4

clé de peau
BEAUTÉ

CONCEALER N
BROAD SPECTRUM
SPF 27
SUNSCREEN

seamless finish
long-lasting

5g NET WT. .17 OZ.

PRINCIPAL DISPLAY PANEL - 5 g Cartridge Carton - 5

clé de peau
BEAUTÉ

CONCEALER N
BROAD SPECTRUM
SPF 27
SUNSCREEN

seamless finish
long-lasting

5g NET WT. .17 OZ.

PRINCIPAL DISPLAY PANEL - 5 g Cartridge Carton - 7

clé de peau
BEAUTÉ

CONCEALER N
BROAD SPECTRUM
SPF 27
SUNSCREEN

seamless finish
long-lasting

5g NET WT. .17 OZ.

PRINCIPAL DISPLAY PANEL - 5 g Cartridge Carton - 8

clé de peau
BEAUTÉ

CONCEALER N
BROAD SPECTRUM
SPF 27
SUNSCREEN

seamless finish
long-lasting

5g NET WT. .17 OZ.

PRINCIPAL DISPLAY PANEL - 5 g Cartridge Carton - 9

clé de peau
BEAUTÉ

CONCEALER N
BROAD SPECTRUM
SPF 27
SUNSCREEN

seamless finish
long-lasting

5g NET WT. .17 OZ.

PRINCIPAL DISPLAY PANEL - 5 g Cartridge Carton - 10

clé de peau
BEAUTÉ

CONCEALER N
BROAD SPECTRUM
SPF 27
SUNSCREEN

seamless finish
long-lasting

5g NET WT. .17 OZ.

PRINCIPAL DISPLAY PANEL - 5 g Cartridge Carton - 11

clé de peau
BEAUTÉ

CONCEALER N
BROAD SPECTRUM
SPF 27
SUNSCREEN

seamless finish
long-lasting

5g NET WT. .17 OZ.

PRINCIPAL DISPLAY PANEL - 5 g Cartridge Carton - 12

clé de peau
BEAUTÉ

CONCEALER N
BROAD SPECTRUM
SPF 27
SUNSCREEN

seamless finish
long-lasting

5g NET WT. .17 OZ.

PRINCIPAL DISPLAY PANEL - 5 g Cartridge Carton - 13

clé de peau
BEAUTÉ

CONCEALER N
BROAD SPECTRUM
SPF 27
SUNSCREEN

seamless finish
long-lasting

5g NET WT. .17 OZ.